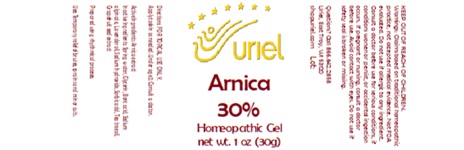 DRUG LABEL: Arnica 30
NDC: 48951-1399 | Form: GEL
Manufacturer: Uriel Pharmacy, Inc
Category: homeopathic | Type: HUMAN OTC DRUG LABEL
Date: 20250221

ACTIVE INGREDIENTS: ARNICA MONTANA FLOWER 1 [hp_X]/1 g
INACTIVE INGREDIENTS: CITRUS PARADISI SEED; LAVENDER OIL; WATER; BORIC ACID; SODIUM HYDROXIDE; GLYCERIN; SODIUM ALGINATE; SORBIC ACID; TEA TREE OIL

Arnica 30

INDICATIONS AND USAGE

Directions: FOR TOPICAL USE ONLY.

DOSAGE AND ADMINISTRATION

Apply to skin as needed. Under age 2: Consult a doctor.

Active Ingredients: Arnica extract

INACTIVE INGREDIENT

Inactive Ingredients: Spring water, Glycerin, Boric acid, Sodium alginate, Lavender oil, Sodium hydroxide, Sorbic acid, Tea tree oil, Grapefruit seed extract

Prepared using rhythmical processes.

PURPOSE

Uses: Temporary relief of bruises, sprains and minor cuts.

KEEP OUT OF REACH OF CHILDREN.

WARNINGS

Warnings: Claims based on traditional homeopathic practice, not accepted medical evidence. Not FDA evaluated. Do not use if allergic to any ingredient. Consult a doctor before use for serious conditions, if conditions worsen or persist, or accidental ingestion occurs. If pregnant or nursing, consult a doctor before use. Avoid contact with eyes. Do not use if safety seal is broken or missing.

Questions? Call 866.642.2858
Uriel, East Troy, WI 53120
shopuriel.com Lot: